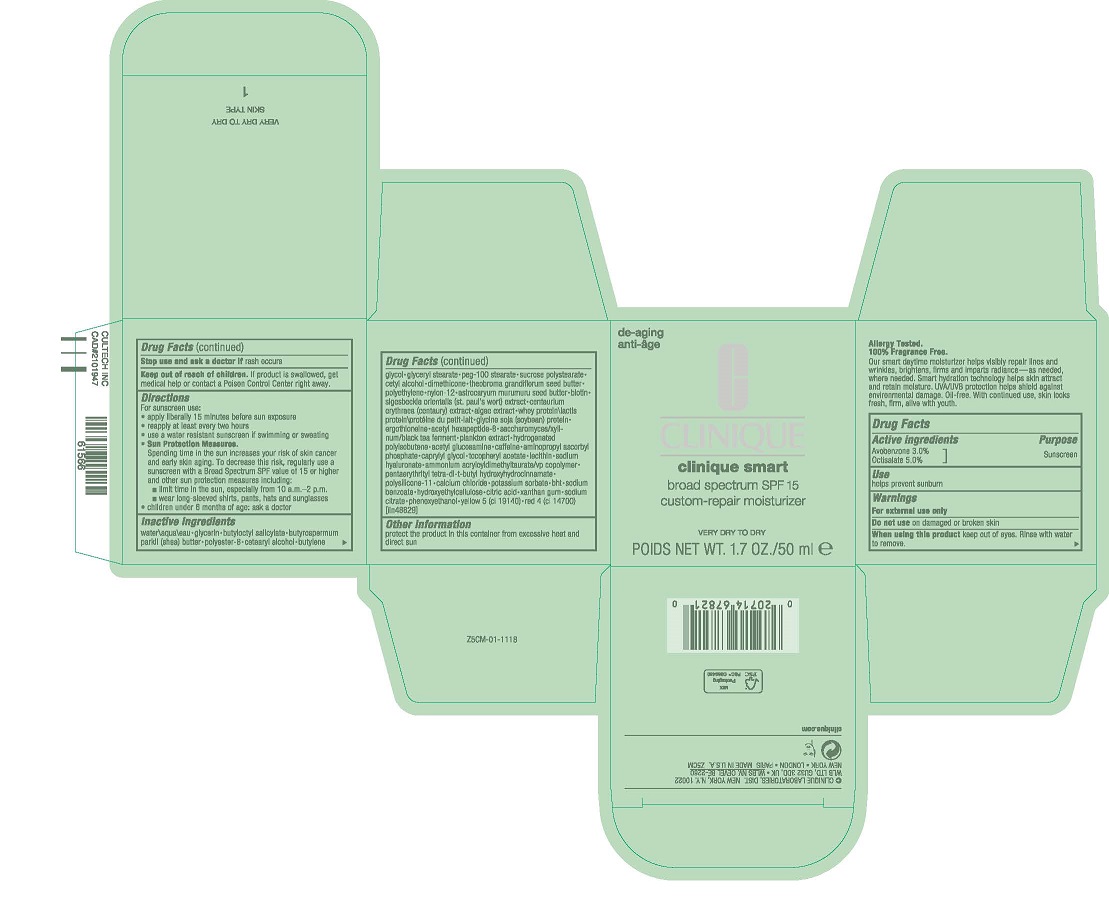 DRUG LABEL: CLINIQUE SMART CUSTOM REPAIR MOISTURIZER BROAD SPECTRUM SPF 15 - VERY DRY/DRY
NDC: 49527-048 | Form: CREAM
Manufacturer: CLINIQUE LABORATORIES LLC
Category: otc | Type: HUMAN OTC DRUG LABEL
Date: 20231005

ACTIVE INGREDIENTS: AVOBENZONE 30 mg/1 mL; OCTISALATE 50 mg/1 mL
INACTIVE INGREDIENTS: WHEY; CALCIUM CHLORIDE; BUTYLATED HYDROXYTOLUENE; DICTYOPTERIS POLYPODIOIDES; HYDROXYETHYL CELLULOSE, UNSPECIFIED; CETOSTEARYL ALCOHOL; SIGESBECKIA ORIENTALIS WHOLE; POLYESTER-8 (1400 MW, CYANODIPHENYLPROPENOYL CAPPED); SUCROSE TETRASTEARATE TRIACETATE; WATER; GLYCERIN; BUTYLOCTYL SALICYLATE; SHEA BUTTER; BUTYLENE GLYCOL; GLYCERYL MONOSTEARATE; PEG-100 STEARATE; CETYL ALCOHOL; DIMETHICONE; THEOBROMA GRANDIFLORUM SEED BUTTER; HIGH DENSITY POLYETHYLENE; NYLON-12; ASTROCARYUM MURUMURU SEED BUTTER; GREEN TEA LEAF; BIOTIN; CENTAURIUM ERYTHRAEA; TAMARIND SEED; SOYBEAN; ERGOTHIONEINE; ACETYL HEXAPEPTIDE-8; N-ACETYLGLUCOSAMINE; CAFFEINE; AMINOPROPYL ASCORBYL PHOSPHATE; CAPRYLYL GLYCOL; .ALPHA.-TOCOPHEROL ACETATE; DIMETHICONE/VINYL DIMETHICONE CROSSPOLYMER (SOFT PARTICLE); HYALURONATE SODIUM; AMMONIUM ACRYLOYLDIMETHYLTAURATE/VP COPOLYMER; PENTAERYTHRITOL TETRAKIS(3-(3,5-DI-TERT-BUTYL-4-HYDROXYPHENYL)PROPIONATE); POTASSIUM SORBATE; SODIUM BENZOATE; CITRIC ACID MONOHYDRATE; XANTHAN GUM; SODIUM CITRATE, UNSPECIFIED FORM; PHENOXYETHANOL; FD&C YELLOW NO. 5; FD&C RED NO. 4

CLINIQUE SMART CUSTOM REPAIR MOISTURIZER BROAD SPECTRUM SPF 15 - VERY DRY/DRY

Drug Facts

Active ingredients

Avobenzone 3%
Octisalate 5%

Purpose

Sunscreen

Use

helps prevent sunburn

Warnings

For external use only

Do not use on damaged or broken skin

When using this product keep out of eyes. Rinse with water to remove.

Stop use and ask a doctor if rash occurs

Keep out of reach of children. If product is swallowed, get medical help or contact a Poison Control Center right away.

Directions

For sunscreen use:

- apply liberally 15 minutes before sun exposure
- reapply at least every two hours
- use a water resistant sunscreen if swimming or sweating
- Sun Protection Measures.
  Spending time in the sun increases your risk of skin cancer and early skin aging. To decrease this risk, regularly use a sunscreen with a Broad Spectrum SPF value of 15 or higher and other sun protection measures including:
  - limit time in the sun, especially from 10 a.m.–2 p.m.
  - wear long-sleeved shirts, pants, hats and sunglasses
- children under 6 months of age: ask a doctor

Inactive ingredients

water\aqua\eau • glycerin • butyloctyl salicylate • butyrospermum parkii (shea butter) • polyester-8 • cetearyl alcohol • butylene glycol • glyceryl stearate • peg-100 stearate • sucrose polystearate • cetyl alcohol • dimethicone • theobroma grandiflorum seed butter • polyethylene • nylon-12 • astrocaryum murumuru seed butter • camellia sinensis leaf extract • biotin • sigesbeckia orientalis (st. paul's wort) extract • centaurium erythraea (centaury) extract • algae extract • tamarindus indica seed extract • whey protein\lactis protein\protéine du petit-lait • glycine soja (soybean) protein • ergothioneine • acetyl hexapeptide-8 • saccharomyces ferment filtrate • plankton extract • hydrogenated polyisobutene • acetyl glucosamine • caffeine • aminopropyl ascorbyl phosphate • caprylyl glycol • tocopheryl acetate • lecithin • sodium hyaluronate • ammonium acryloyldimethyltaurate/vp copolymer • pentaerythrityl tetra-di-t-butyl hydroxyhydrocinnamate • polysilicone-11 • potassium sorbate • sodium benzoate • hydroxyethylcellulose • citric acid • xanthan gum • sodium citrate • phenoxyethanol • yellow 5 (ci 19140) • red 4 (ci 14700) [iln41876]

Other information

protect the product in this container from excessive heat and direct sun

PRINCIPAL DISPLAY PANEL - 50 ml Jar Carton

de-aging

CLINIQUE

clinique smart
broad spectrum SPF 15
custom-repair moisturizer

VERY DRY TO DRY

POIDS NET WT. 1.7 OZ./50 ml e